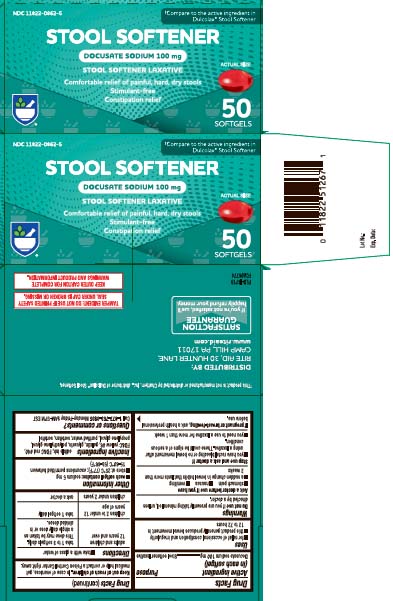 DRUG LABEL: Stool Softener Laxative
NDC: 11822-0862 | Form: CAPSULE
Manufacturer: Rite Aid Corporation
Category: otc | Type: HUMAN OTC DRUG LABEL
Date: 20240508

ACTIVE INGREDIENTS: DOCUSATE SODIUM 100 mg/1 1
INACTIVE INGREDIENTS: FD&C RED NO. 40; FD&C YELLOW NO. 6; GELATIN; SORBITAN; POLYETHYLENE GLYCOL, UNSPECIFIED; PROPYLENE GLYCOL; WATER; SORBITOL; GLYCERIN

DRUG FACTS

Active ingredient (in each softgel)

Docusate Sodium 100 mg

Purpose

Stool softener laxative

Uses

- for temporary relief of occasional constipation and irregularity
- this product generally produces bowel movement in 12 to 72 hours

Warnings

Do not use

if you are presently taking mineral oil, unless directed by a doctor

Ask a doctor before use if

- stomach pain
- nausea
- vomiting
- noticed a sudden change in bowel habits that lasts over 2 weeks

Stop use and ask a doctor if

- you have rectal bleeding or fail to have a bowel movement after using a laxative. These could be a sign of a serious condition
- you need to use a laxative for more than 1 week

If pregnant or breast-feeding,

ask a health care professional before use.

Keep out of reach of children.

In case of overdose, get medical help or contact a Poison Control Center right away.

Directions

- take with a glass of water

adults and children 12 over and over | take 1-3 softgels daily. This dose may be taken as a single daily dose or in divided doses.
children 2 to under 12 years of age | take 1 softgel daily
children under 2 years | ask a doctor

Other information

- each softgel contains: sodium 5 mg
- store at 25ºC (77ºF); excursion permitted between 15-30ºC (59-86ºF)

Inactive ingredients

edible ink, FD&C Red #40, FD&C Yellow #6, gelatin, glycerin, polyethylene glycol, propylene glycol, purified water sorbitan, sorbitol

Questions or comments?

Call 1-877-753-3935 Monday-Friday 9AM-5PM EST

Principal Display Panel

Compare to the active ingredient in Dulcolax® Stool Softener†

STOOL SOFTENER

DOCUSATE SODIUM, 100 mg

Comfortable relief of painful, hard, dry stools

Stimulant-free

Constipation relief

SOFTGELS

†This product is not manufactured or distributed by Boehringer Ingelheim Pharmaceuticals, Inc., distributor of DulcoEase®.

TAMPER EVIDENT: DO NOT USE IF PRINTED SAFETY SEAL UNDER CAP IS BROKEN OR MISSING.

KEEP OUTER CARTON FOR COMPLETE WARNINGS AND PRODUCT INFORMATION

DISTRIBUTED BY:

RITE AID, 30 HUNTER LANE,

CAMP HILL, PA 17011

www.riteaid.com

Product Label

RITE AID Stool Softener